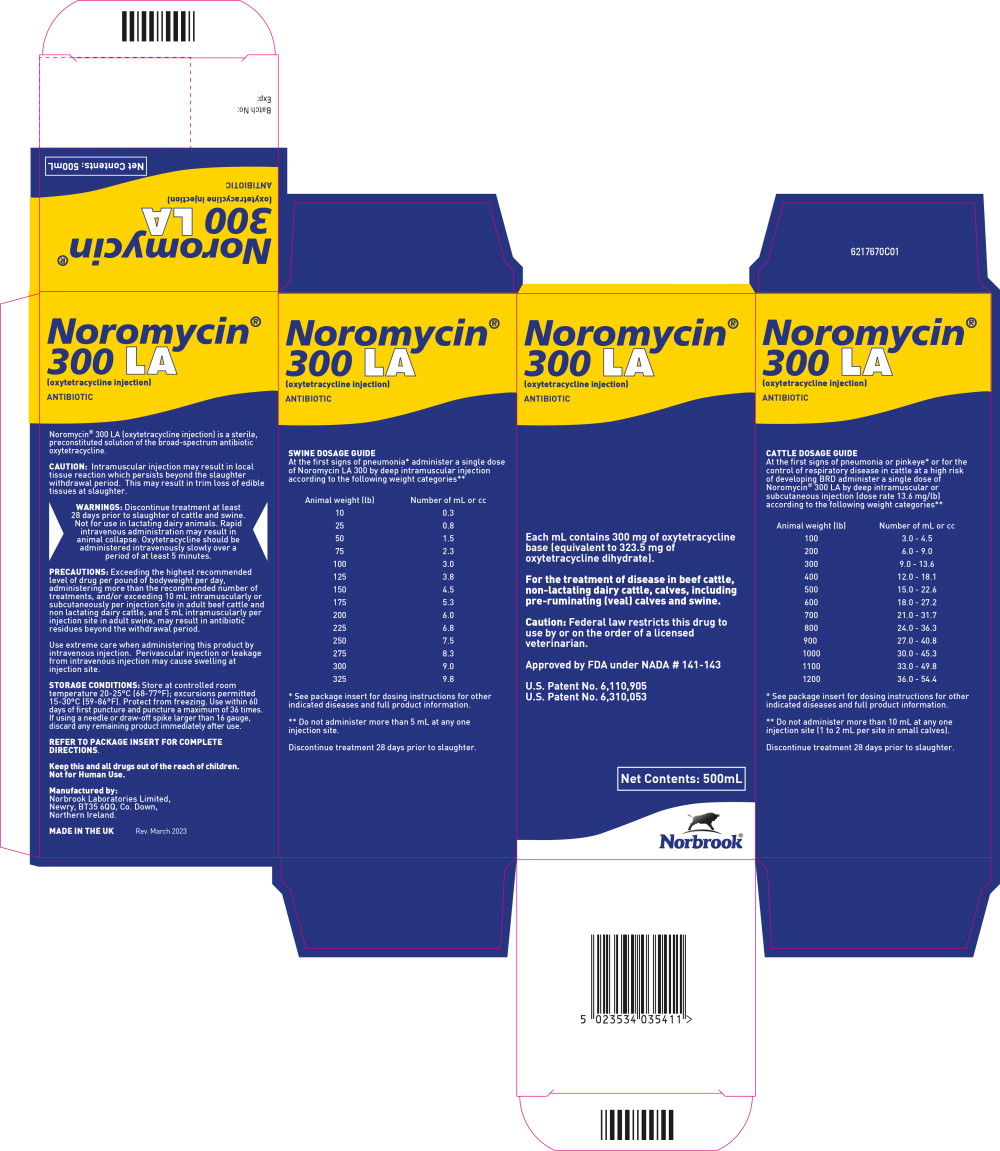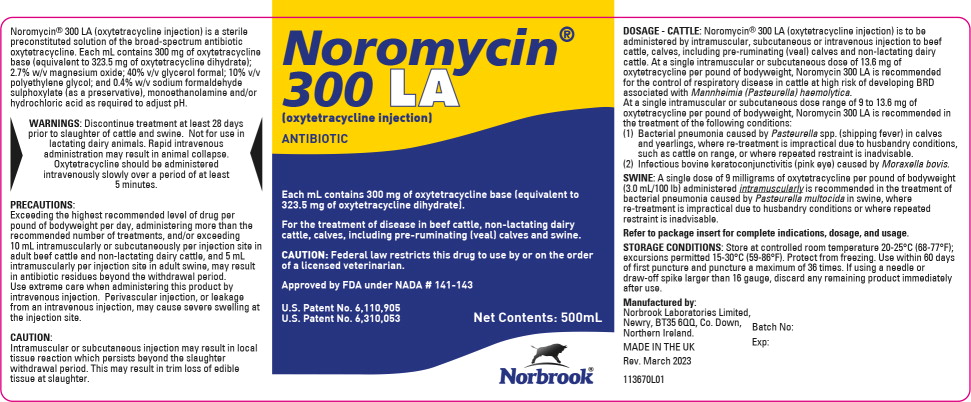 DRUG LABEL: Noromycin 300 LA
NDC: 55529-015 | Form: INJECTION, SOLUTION
Manufacturer: Norbrook Laboratories Limited
Category: animal | Type: PRESCRIPTION ANIMAL DRUG LABEL
Date: 20230525

ACTIVE INGREDIENTS: oxytetracycline 300 mg/1 mL
INACTIVE INGREDIENTS: glycerol formal; polyethylene glycol, unspecified; magnesium oxide; sodium formaldehyde sulfoxylate

Approved by FDA under NADA # 141-143

Noromycin®
300 LA
(oxytetracycline injection)

ANTIBIOTIC

Each mL contains 300 mg of oxytetracycline base (equivalent to 323.5 mg of oxytetracycline dihydrate).

For Use in Beef Cattle, Non-lactating Dairy Cattle, Calves, Including Pre-ruminating (Veal) Calves and Swine.

READ ENTIRE BROCHURE CAREFULLY BEFORE USING THIS PRODUCT.

Caution: Federal law restricts this drug to use by or on the order of a licensed veterinarian.

INTRODUCTION:

Noromycin 300 LA (oxytetracycline injection) is a sterile, ready to use solution of the broad-spectrum antibiotic oxytetracycline dihydrate. Oxytetracycline is an antimicrobial agent that is effective in treatment of a wide range of diseases caused by susceptible gram-positive and gram-negative bacteria. The antibiotic activity of oxytetracyline is not appreciably diminished in the presence of body fluids, serum or exudates.

INGREDIENTS:

Noromycin 300 LA (oxytetracycline injection) is a sterile, pre-constituted solution of the broad-spectrum antibiotic oxytetracycline dihydrate. Each mL contains 300 mg of oxytetracycline base (equivalent to 323.5 mg of oxytetracycline dihydrate), 40% (v/v) glycerol formal, 10% (v/v) polyethylene glycol 200, 2.7% (w/v) magnesium oxide, 0.4% (w/v) sodium formaldehyde sulphoxylate (as a preservative) and monoethanolamine (as required to adjust pH).

INDICATIONS:

Noromycin 300 LA is intended for use in treatment for the following diseases when due to oxytetracycline-susceptible organisms:

Beef cattle, non-lactating dairy cattle, calves, including pre-ruminating (veal) calves:

Noromycin 300 LA is indicated in the treatment of pneumonia and shipping fever complex associated with Pasteurella spp., and Histophilus spp. Noromycin 300 LA is indicated for the treatment of infectious bovine keratoconjunctivitis (pink eye) caused by Moraxella bovis, foot-rot and diphtheria caused by Fusobacterium necrophorum; bacterial enteritis (scours) caused by Escherichia coli; wooden tongue caused by Actinobacillus lignieresii; leptospirosis caused by Leptospira pomona; and wound infections and acute metritis caused by strains of staphylococcal and streptococcal organisms sensitive to oxytetracycline. Also, it is indicated for the control of respiratory disease in cattle at high risk of developing BRD associated with Mannheimia (Pasteurella) haemolytica.

Swine:

Noromycin 300 LA is indicated in the treatment of bacterial enteritis (scours, colibacillosis) caused by Escherichia coli; pneumonia caused by Pasteurella multocida; and leptospirosis caused by Leptospira pomona.

In sows Noromycin 300 LA is indicated as an aid in control of infectious enteritis (baby pig scours, colibacillosis) in suckling pigs caused by Escherichia coli.

PHARMACOLOGY:

Oxytetracycline is derived from the metabolic activity of the actinomycete, Streptomyces rimosus. Oxytetracycline is an antimicrobial agent that is effective in the treatment of a wide range of diseases caused by susceptible gram-positive and gram-negative bacteria.

The antibiotic activity of oxytetracycline is not appreciably diminished in the presence of body fluids, serum or exudates.

Studies have shown that the half-life of oxytetracycline in blood following intramuscular treatment with Noromycin 300 LA at 5 mg per pound of bodyweight is approximately 23 hours in cattle and 18 hours in swine.

Studies have shown when Noromycin 300 LA is administered once intramuscularly to cattle or swine at 9 mg per pound of bodyweight, blood oxytetracycline concentration of greater than 0.2 mcg/mL have been observed for 3 to 4 days.

Studies have shown when Noromycin 300 LA is administered once intramuscularly or subcutaneously to cattle at 13.6 mg per pound of bodyweight, blood oxytetracycline concentration of greater than 0.2 mcg/mL have been observed for at least 7 to 8 days.

DOSAGE AND ADMINISTRATION:

Beef cattle, non-lactating dairy cattle, calves, including pre-ruminating (veal) calves:

A single intramuscular or subcutaneous dosage of 13.6 mg of oxytetracycline per pound of bodyweight, Noromycin 300 LA is recommended for the control of respiratory disease in cattle at high risk of developing BRD associated with Mannheimia (Pasteurella) haemolytica.

At a single intramuscular or subcutaneous dose range of 9 to 13.6 mg of oxytetracycline per pound of bodyweight, Noromycin 300 LA is recommended in the treatment of the following conditions:

1. Bacterial pneumonia caused by Pasteurella spp (shipping fever) in calves and yearlings where retreatment is impractical due to husbandry conditions, such as cattle on range, or where their repeated restraint is inadvisable.
2. Infectious bovine kertaconjunctivitis (pink eye) caused by Moraxella bovis.

For other indications Noromycin 300 LA is to be administered intramuscularly, subcutaneously or intravenously at a level of 3 to 5 mg of oxytetracycline per pound of bodyweight per day. In treatment of foot-rot and advanced cases of other indicated diseases, a dosage level of 5 mg per pound of bodyweight per day is recommended. Treatment should be continued 24 to 48 hours following remission of disease signs, however, not to exceed a total of four (4) consecutive days.

If improvement is not noted within 24 to 48 hours of the beginning of treatment, diagnosis and therapy should be re-evaluated.

Do not administer intramuscularly in the neck of small calves due to lack of sufficient muscle mass.

Use extreme care when administering this product by intravenous injection. Perivascular injection or leakage from an intravenous injection may cause severe swelling at the injection site.

Swine:

A single dosage of 9 mg of oxytetracycline per pound of bodyweight administered intramuscularly is recommended in the treatment of bacterial pneumonia caused by Pasteurella multocida in swine, where retreatment is impractical due to husbandry conditions or where repeated restraint is inadvisable.

For the treatment of bacterial enteritis, pneumonia, and leptospirosis, administer 3 to 5 mg of oxytetracycline per pound of bodyweight per day by intramuscular injection. Treatment should be continued 24 to 48 hours following remission of disease signs; however, not to exceed a total of four (4) consecutive days. If improvement is not noted within 24 to 48 hours of the beginning of treatment, diagnosis and therapy should be re-evaluated.

For sows, administer once intramuscularly 3 mg of oxytetracycline per pound of bodyweight approximately eight (8) hours before farrowing or immediately after completion of farrowing as an aid in the control of infectious enteritis in baby pigs.

For swine weighing 25 lbs of bodyweight and under, Noromycin 300 LA should be administered undiluted for treatment at 9 mg/lb but should be administered diluted for treatment at 3 or 5 mg/lb.

 | 9 mg dosage of undiluted Noromycin 300 LA | 3 or 5 mg/lb volume of diluted Noromycin 300 LA
Bodyweight | 9 mg/lb | 3 mg/lb | Dilution* | 5 mg/lb
5 lb | 0.15 mL | 0.4 mL | 37.5 mg/mL | 0.7 mL
10 lb | 0.30 mL | 0.6 mL | 50 mg/mL | 1.0 mL
25 lb | 0.75 mL | 1.0 mL | 75 mg/mL | 1.7 mL
* To prepare dilutions, add one part of Noromycin 300 LA to three (3), five (5) or seven (7) parts of the sterile water, or 5% dextrose solution as indicated; the diluted product should be used immediately.

PRECAUTIONS:

Exceeding the highest recommended level of drug per pound of bodyweight per day, administering more than the recommended number of treatments, and/or exceeding 10 mL intramuscularly or subcutaneously per injection site in adult beef cattle and non-lactating dairy cattle and 5 mL intramuscularly per injection site in adult swine, may result in antibiotic residues beyond the withdrawal period.

Consult with your veterinarian prior to administering this product in order to determine the proper treatment required in the event of an adverse reaction. At the first sign of any adverse reaction, discontinue use of the product and seek the advice of your veterinarian. Some of the reactions may be attributable either to anaphylaxis (an allergic reaction) or to cardiovascular collapse of unknown cause.

Shortly after injection treated animals may have transient hemoglobinuria resulting in darkened urine.

As with all antibiotic preparations, use of this drug may result in overgrowth of non-susceptible organisms, including fungi. The absence of a favourable response following treatment, or the development of new signs or symptoms may suggest an overgrowth of non-susceptible organisms. If superinfections occur, the use of this product should be discontinued and appropriate specific therapy should be instituted.

Since bacteriostatic drugs may interfere with the bactericidal action of penicillin, it is advisable to avoid giving Noromycin 300 LA in conjunction with penicillin.

STORAGE CONDITIONS:

Store at controlled room temperature 20-25°C (68-77°F); excursions permitted 15-30°C (59-86°F). Protect from freezing. For 100 mL size: Use within 60 days of first puncture and puncture a maximum of 24 times. For 250 mL and 500 mL sizes: Use within 60 days of first puncture and puncture a maximum of 36 times. If using a needle or draw-off spike larger than 16 gauge, discard any remaining product immediately after use.

WARNINGS:

WARNINGS: Discontinue treatment at least 28 days prior to slaughter of cattle and swine.

Not for use in lactating dairy animals. Rapid intravenous administration may result in animal collapse. Oxytetracycline should be administered intravenously slowly over a period of at least 5 minutes.

The Safety Data Sheet (SDS) contains more detailed occupational safety information. To report suspected adverse drug events, for technical assistance or to obtain a copy of the Safety Data Sheet (SDS), contact Norbrook at 1-866-591-5777.

CAUTION:

Intramuscular or subcutaneous injection may result in local tissue reactions which persists beyond the slaughter withdrawal period. This may result in trim loss of edible tissue at slaughter.

Intramuscular injection in the rump area may cause mild temporary lameness associated with swelling at the injection site. Subcutaneous injection in the neck area may cause swelling at the injection site.

ADVERSE REACTIONS:

Reports of adverse reactions associated with oxytetracycline administration include injection site swelling, restlessness, ataxia, trembling, swelling of eyelids, ears, muzzle, anus and vulva (or scrotum and sheath in males), respiratory abnormalities (labored breathing), frothing at the mouth, collapse and possibly death. Some of these reactions may be attributed either to anaphylaxis (an allergic reaction) or to cardiovascular collapse of unknown cause. To report a suspected adverse reaction call 1-866-591-5777.

PRESENTATION:

Noromycin 300 LA is available in 100 mL, 250 mL and 500 mL vials.

Livestock Drug - Not for Human Use.

Manufactured by:

Norbrook Laboratories Limited,
Newry, BT35 6QQ, Co. Down,
Northern Ireland.

MADE IN THE UK

U.S. Patent No. 6,110,905

U.S. Patent No. 6,310,053

013670I01

March 2023

Norbrook®

Principal Display Panel – 500 mL Carton Label

Noromycin®
300 LA
(oxytetracycline injection)

ANTIBIOTIC

Each mL contains 300 mg of oxytetracycline
base (equivalent to 323.5 mg of
oxytetracycline dihydrate).

For the treatment of disease in beef cattle,
non-lactating dairy cattle, calves, including
pre-ruminating (veal) calves and swine.

Caution: Federal law restricts this drug to
use by or on the order of a licensed
veterinarian.

Approved by FDA under NADA # 141-143

U.S. Patent No. 6,110,905

U.S. Patent No. 6,310,053

Net Contents: 500mL

Norbook®

Principal Display Panel – 500 mL Vial Label

Noromycin®
300 LA
(oxytetracycline injection)

ANTIBIOTIC

Each mL contains 300 mg of oxytetracycline base (equivalent to
323.5 mg of oxytetracycline dihydrate).

For the treatment of disease in beef cattle, non-lactating dairy
cattle, calves, including pre-ruminating (veal) calves and swine.

CAUTION: Federal law restricts this drug to use by or on the order
of a licensed veterinarian.

Approved by FDA under NADA # 141-143

U.S. Patent No. 6,110,905

U.S. Patent No. 6,310,053

Net Contents: 500mL

Norbook®